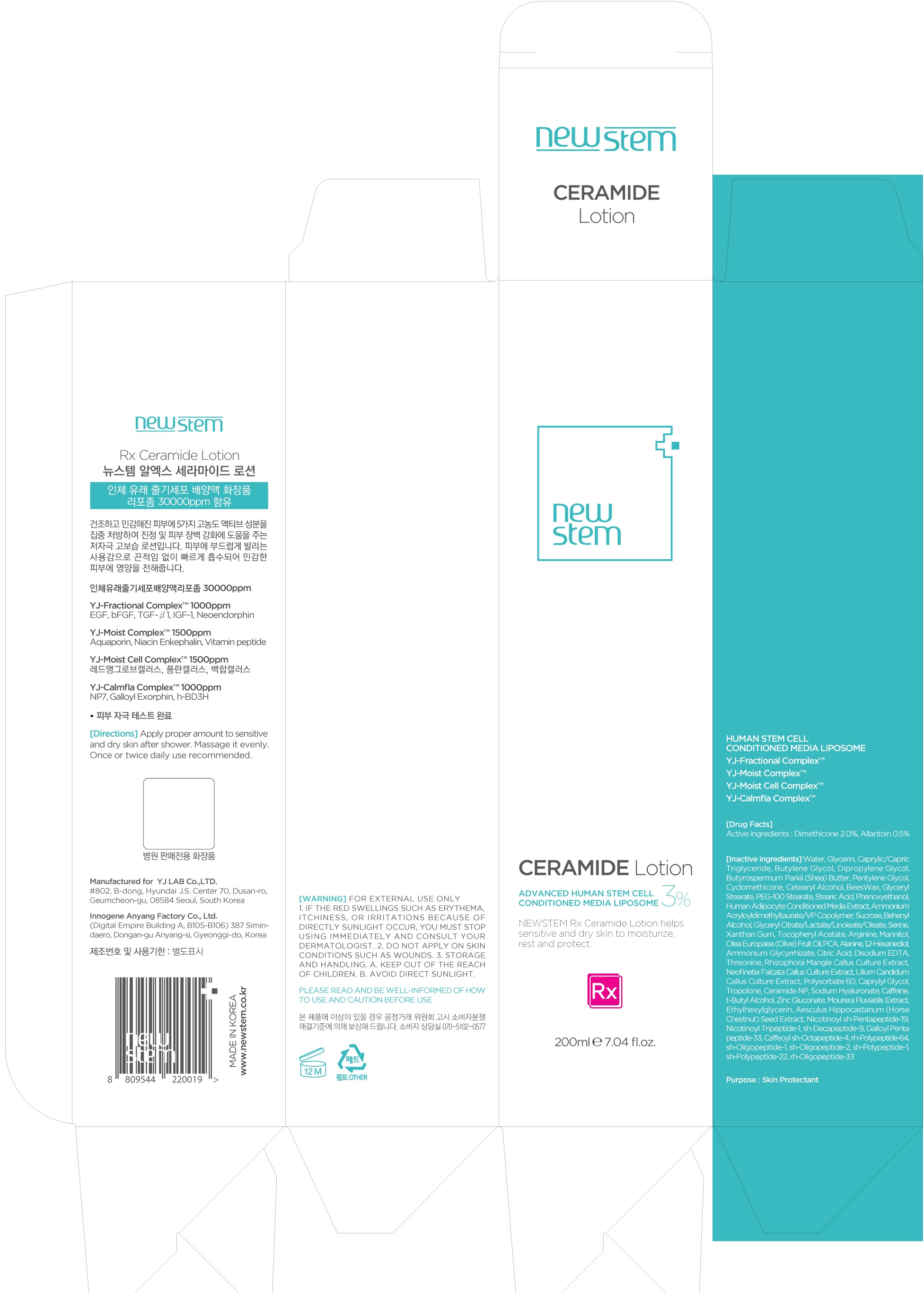 DRUG LABEL: NEWSTEM Rx Ceramide
NDC: 71759-020 | Form: LOTION
Manufacturer: Yj Lab Co., Ltd.
Category: otc | Type: HUMAN OTC DRUG LABEL
Date: 20200410

ACTIVE INGREDIENTS: Dimethicone 4.0 g/200 mL; Allantoin 1.0 g/200 mL
INACTIVE INGREDIENTS: Water; Glycerin

ACTIVE INGREDIENT

Active ingredients: Dimethicone 2.0%, Allantoin 0.5%

INACTIVE INGREDIENT

Inactive ingredients: Water, Glycerin, Caprylic/Capric Triglyceride, Butylene Glycol, Dipropylene Glycol, Butyrospermum Parkii (Shea) Butter, Pentylene Glycol, Cyclomethicone, Cetearyl Alcohol, BeesWax, Glyceryl Stearate, PEG-100 Stearate, Stearic Acid, Phenoxyethanol, Human Adipocyte Conditioned Media Extract, Ammonium Acryloyldimethyltaurate/VP Copolymer, Sucrose, Behenyl Alcohol, Glyceryl Citrate/Lactate/Linoleate/Oleate, Serine, Xanthan Gum, Tocopheryl Acetate, Arginine, Mannitol, Olea Europaea (Olive) Fruit Oil, PCA, Alanine, 1,2-Hexanediol, Ammonium Glycyrrhizate, Citric Acid, Disodium EDTA, Threonine, Rhizophora Mangle Callus Culture Extract, Neofinetia Falcata Callus Culture Extract, Lilium Candidum Callus Culture Extract, Polysorbate 60, Caprylyl Glycol, Tropolone, Ceramide NP, Sodium Hyaluronate, Caffeine, t-Butyl Alcohol, Zinc Gluconate, Mourera Fluviatilis Extract, Ethylhexylglycerin, Aesculus Hippocastanum (Horse Chestnut) Seed Extract, Nicotinoyl sh-Pentapeptide-19, Nicotinoyl Tripeptide-1, sh-Decapeptide-9, Galloyl Pentapeptide-33, Caffeoyl sh-Octapeptide-4, rh-Polypeptide-64, sh-Oligopeptide-1, sh-Oligopeptide-2, sh-Polypeptide-1, sh-Polypeptide-22, rh-Oligopeptide-33

PURPOSE

Purpose: Skin Protectant

WARNINGS

Warnings: For external use only 1. If the Red swellings such as erythema, itchiness, or irritations because of directly sunlight occur, you must stop using immediately and Consult your dermatologist. 2. Do not apply on skin conditions such as wounds. 3. Storage and Handling. a. Keep out of the reach of children. b. Avoid direct sunlight.

KEEP OUT OF REACH OF CHILDREN

Uses

Uses: NEWSTEM Rx Ceramide Lotion helps sensitive and dry skin to moisturize, rest and protect.

Directions

Directions: Apply proper amount to sensitive and dry skin after shower. Massage it evenly. Once or twice daily use recommended.